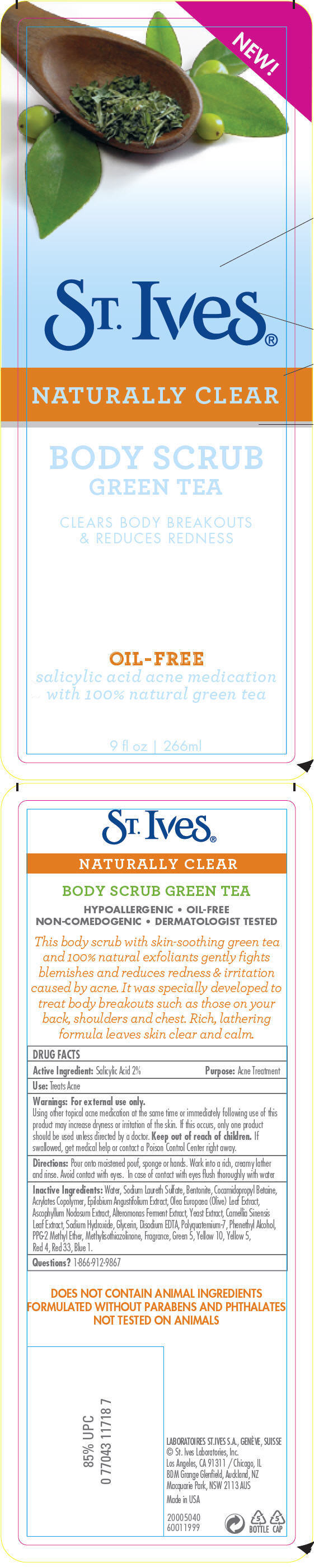 DRUG LABEL: ST. IVES 
NDC: 54726-0500 | Form: EMULSION
Manufacturer: Cosmetic Laboratories of America
Category: otc | Type: HUMAN OTC DRUG LABEL
Date: 20110302

ACTIVE INGREDIENTS: Salicylic Acid 0.02 mL/1 mL
INACTIVE INGREDIENTS: Water; Sodium Laureth Sulfate; Bentonite; Cocamidopropyl Betaine; Sodium Hydroxide; Glycerin; Edetate Disodium; Phenylethyl Alcohol; Olea Europaea Leaf; Ascophyllum Nodosum; Methylisothiazolinone; D&C Green No. 5; D&C Yellow No. 10; Yeast; Green Tea Leaf; Fd&C Yellow No. 5; Fd&C Red No. 4; Fd&C Blue No. 1; D&C Red No. 33

St. Ives®
NATURALLY CLEAR
BODY SCRUB
GREEN TEA

Active Ingredient

Salicylic Acid 2%

Purpose

Acne Treatment

Use

Treats Acne

Warnings

For external use only.

Using other topical acne medication at the same time or immediately following use of this product may increase dryness or irritation of the skin. If this occurs, only one product should be used unless directed by a doctor.

Keep out of reach of children. If swallowed, get medical help or contact a Poison Control Center right away.

Directions

Pour onto moistened pouf, sponge or hands. Work into a rich, creamy lather and rinse. Avoid contact with eyes. In case of contact with eyes flush thoroughly with water

Inactive Ingredients

Water, Sodium Laureth Sulfate, Bentonite, Cocamidopropyl Betaine, Acrylates Copolymer, Epilobium Angustifolium Extract, Olea Europaea (Olive) Leaf Extract, Ascophyllum Nodosum Extract, Alteromonas Ferment Extract, Yeast Extract, Camellia Sinensis Leaf Extract, Sodium Hydroxide, Glycerin, Disodium EDTA, Polyquaternium-7, Phenethyl Alcohol, PPG-2 Methyl Ether, Methylisothiazolinone, Fragrance, Green 5, Yellow 10, Yellow 5, Red 4, Red 33, Blue 1.

Questions?

1-866-912-9867

PRINCIPAL DISPLAY PANEL - 266 mL Bottle Label

NEW!

St. Ives®

NATURALLY CLEAR

BODY SCRUB
GREEN TEA

CLEARS BODY BREAKOUTS
& REDUCES REDNESS

OIL-FREE
salicylic acid acne medication
with 100% natural green tea

9 fl oz | 266ml